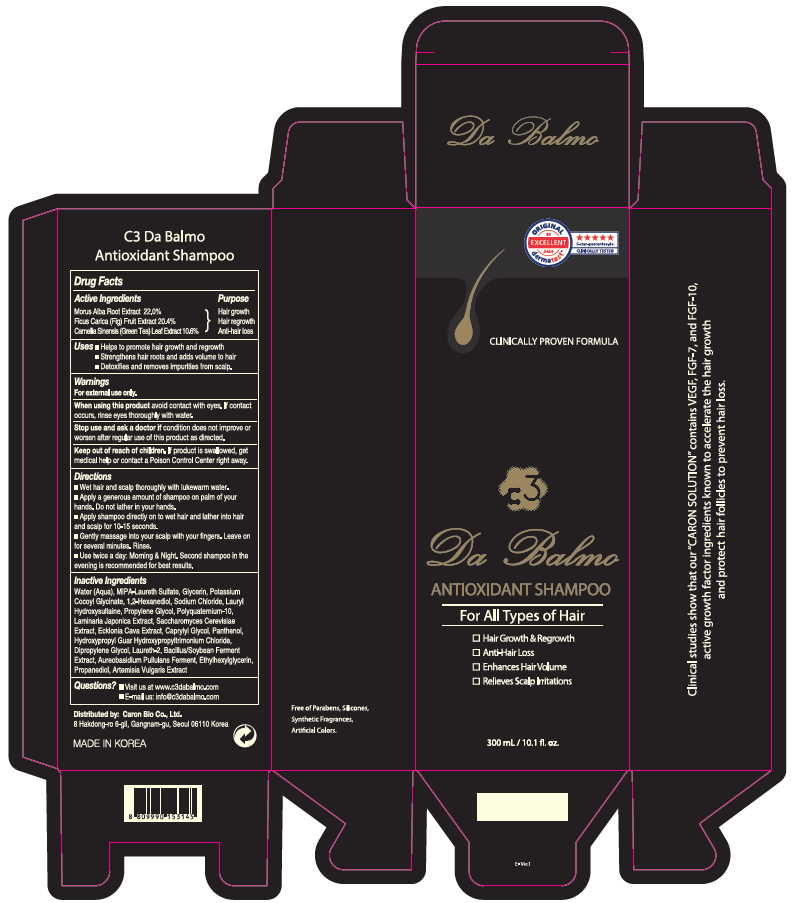 DRUG LABEL: C3 Da Balmo Antioxidant
NDC: 73862-301 | Form: SHAMPOO
Manufacturer: E.CIS COSMETIC.,Co.Ltd
Category: homeopathic | Type: HUMAN OTC DRUG LABEL
Date: 20210416

ACTIVE INGREDIENTS: CAMELLIA SINENSIS ROOT 10.6 mg/1 mL; MORUS ALBA ROOT 22 mg/1 mL; FICUS CARICA WHOLE 20.35 mg/1 mL
INACTIVE INGREDIENTS: POTASSIUM COCOYL GLYCINATE; ETHYLHEXYLGLYCERIN; CAPRYLYL GLYCOL; SODIUM CHLORIDE; LAURYL HYDROXYSULTAINE; LAMINARIA JAPONICA; SACCHAROMYCES CEREVISIAE; GLYCERIN; 1,2-HEXANEDIOL; WATER; PANTHENOL; DIPROPYLENE GLYCOL; PROPANEDIOL; ARTEMISIA VULGARIS WHOLE; LAURETH-2

C3 Da Balmo Shampoo

Active Ingredient

Morus Alba Root Extract 22.0%
Ficus Carica (Fig) Fruit Extract 20.4%
Camellia Sinensis (Green Tea) Leaf Extract 10.6%

Purpose

Hair growth
Hair regrowth
Anti-hair loss

Uses

- Helps to promotes hair growth and regrowth
- Strengthens hair root and adds volume to hair
- Detoxifies and removes impurities from scalp

Warnings

For external use only.

When using this product avoid contact with eyes. If contact occurs, rinse eyes thoroughly with water.

Stop use and ask a doctor if condition does not improve or worsen after regular use of this product as directed

Keep out of reach of children. If product is swallowed, get medical help or contact a Poison Control Center right away.

Directions

- Wet hair and scalp thoroughly with lukewarm water.
- Apply a generous amount of shampoo on palm of you hands. Do not lather in your hands.
- Apply shampoo directly on to wet hair and lather into hair for 10-15 seconds.
- Gently massage into your scalp with your finger. Leave on for several minutes. Rinse.
- Use twice a day: Morning & Night. Second shampoo in the evening is recommended for best results.

Inactive ingredients

Water (Aqua), MIPA-Laureth Sulfate, Glycerin, Potassium Cocoyl Glycinate, 1,2-Hexanediol, Sodium Chloride, Lauryl Hydroxysultaine, Propylene Glycol, Polyquaternium-10, Laminaria Japonica Extract, Saccharomyces Cerevisiae Extract, Ecklonia Cava Extract, Caprylyl Glycol, Panthenol, Hydroxypropyl Guar Hydroxypropyltrimonium Chloride, Dipropylene Glycol, Laureth-2, Bacillus/Soybean Ferment Extract, Aureobasidium Pullulans Ferment, Ethylhexylglycerin, Propanediol, Artemisia Vulgaris Extract

Qustions?

- Visit us at www.c3dabalmo.com
- E-mail us: info@c3dabalmo.com

Principal Display Panel

Original Excellent dermatest
5-star-guarantee.de Clinically Tested

Clinically Proven Formula

C3

Da Balmo

Antioxidant Shampoo

For All Types of Hair

- Hair Growth & Regrowth
- Anti-Hair Loss
- Enhances Hair Volume
- Relieves Scalp Irritations

300 mL / 10.1 fl. oz.

Distributed by: Caron Bio Co., Ltd.
8 Hakdong-ro, 6-gil, Gangnam-gu, Seoul, Republic of Korea

Made in Korea